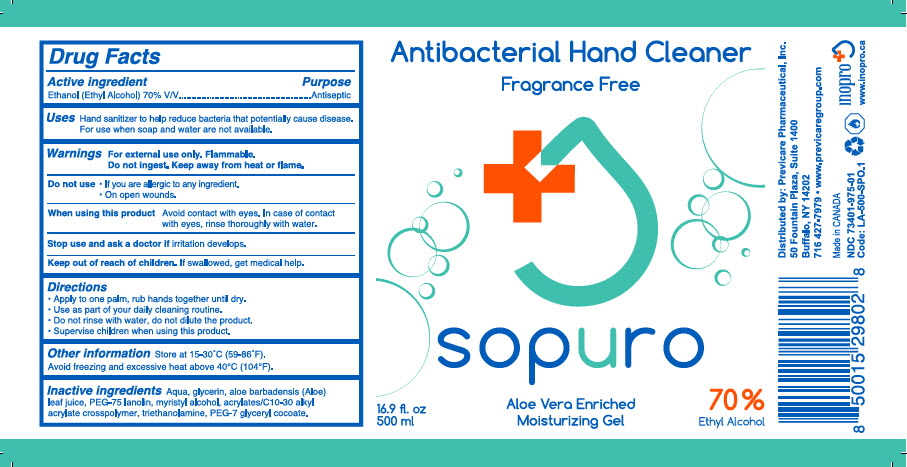 DRUG LABEL: Sopuro 
NDC: 73401-975 | Form: GEL
Manufacturer: Previcare Pharmaceutical, Inc.
Category: otc | Type: HUMAN OTC DRUG LABEL
Date: 20210112

ACTIVE INGREDIENTS: Alcohol 70 mL/100 mL
INACTIVE INGREDIENTS: WATER; GLYCERIN; ALOE VERA LEAF; PEG-75 LANOLIN; MYRISTYL ALCOHOL; CARBOMER INTERPOLYMER TYPE A (ALLYL SUCROSE CROSSLINKED); TROLAMINE; PEG-7 GLYCERYL COCOATE

Sopuro Antibacterial Hand Cleaner

Drug Facts

Active ingredient

Ethanol (Ethyl Alcohol) 70% V/V

Purpose

Antiseptic

Uses

Hand sanitizer to help reduce bacteria that potentially cause disease. For use when soap and water are not available.

Warnings

For external use only. Flammable.

Do not ingest. Keep away from heat or flame.

Do not use

- If you are allergic to any ingredient.
- On open wounds.

When using this product

Avoid contact with eyes. In case of contact with eyes, rinse thoroughly with water.

Stop use and ask a doctor if irritation develops.

Keep out of reach of children. If swallowed, get medical help.

Directions

- Apply to one palm, rub hands together until dry.
- Use as part of your daily cleaning routine.
- Do not rinse with water, do not dilute the product.
- Supervise children when using this product.

Other information

Store at 15-30°C (59-86°F).

Avoid freezing and excessive heat above 40°C (104°F).

Inactive ingredients

Aqua, glycerin, aloe barbadensis (Aloe) leaf juice, PEG-75 lanolin, myristyl alcohol, acrylates/C10-30 alkyl acrylate crosspolymer, triethanolamine, PEG-7 glyceryl cocoate.

Distributed by: Previcare Pharmaceutical, Inc.
50 Fountain Plaza, Suite 1400
Buffalo, NY 14202

PRINCIPAL DISPLAY PANEL - 500 ml Bottle Label

Antibacterial Hand Cleaner

Fragrance Free

sopuro

16.9 fl. oz
500 ml

Aloe Vera Enriched
Moisturizing Gel

70 %
Ethyl Alcohol